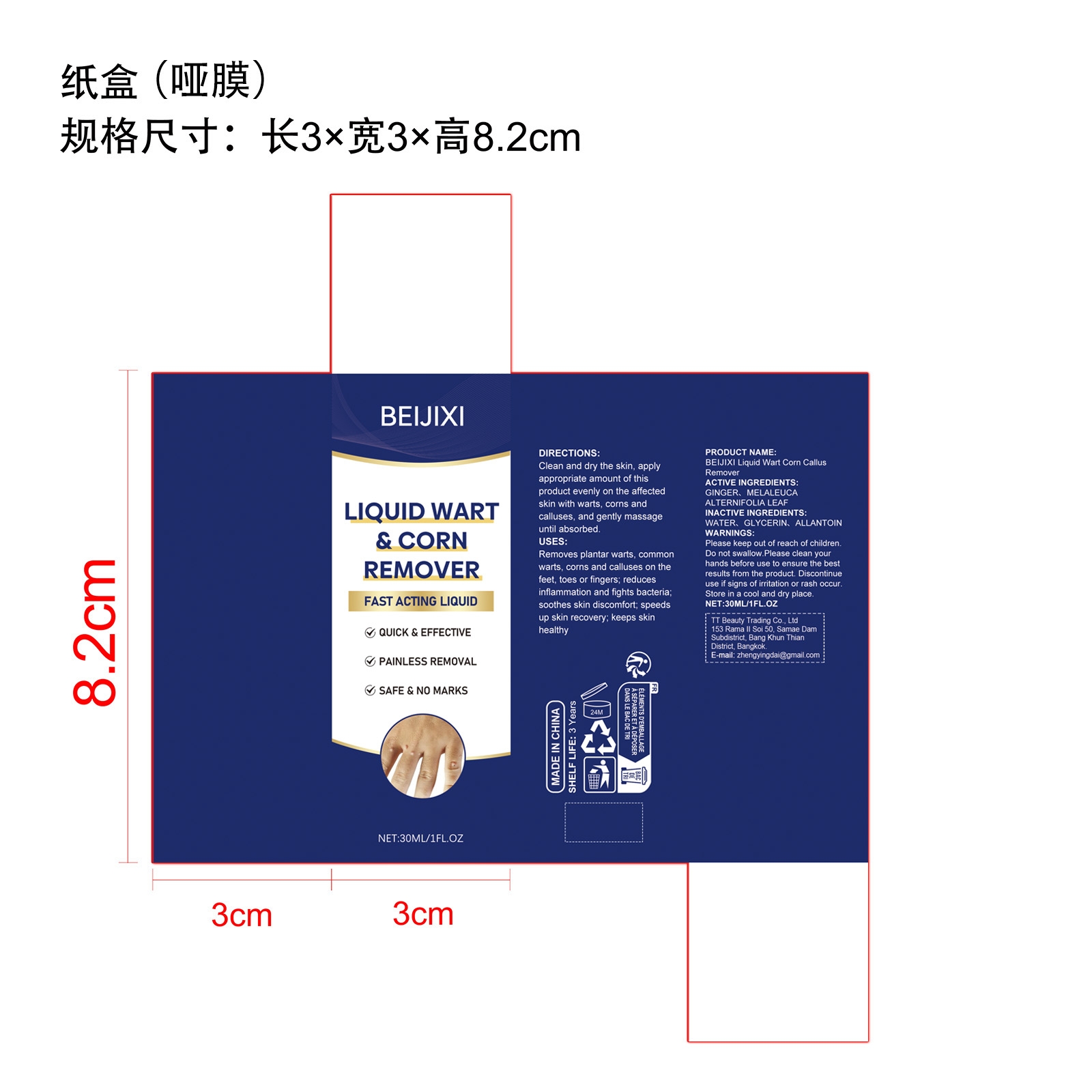 DRUG LABEL: BEIJIXI Liquid Wart Corn Callus Remover
NDC: 85206-003 | Form: LIQUID
Manufacturer: TT Beauty Trading Co., Ltd.
Category: otc | Type: HUMAN OTC DRUG LABEL
Date: 20250826

ACTIVE INGREDIENTS: GINGER 0.15 mg/30 mg; MELALEUCA ALTERNIFOLIA LEAF 0.3 mg/30 mg
INACTIVE INGREDIENTS: WATER 27.45 mg/30 mg; ALLANTOIN 0.6 mg/30 mg; GLYCERIN 1.5 mg/30 mg

ACTIVE INGREDIENT

GINGER、MELALEUCA ALTERNIFOLIA LEAF

WHEN USING

Clean and dry the skin, apply appropriate amount of this product evenly on the affected skin with warts, corns and calluses, and gently massage until absorbed.

PURPOSE

Removes plantar warts, common warts, corns and calluses on the feet, toes or fingers; reduces inflammation and fights bacteria; soothes skin discomfort; speeds up skin recovery; keeps skin healthy

WARNINGS

Please keep out of reach of children. Do not swallow.Please clean your hands before use to ensure the best results from the product. Discontinue use if signs of irritation or rash occur. Store in a cool and dry place.

DO NOT USE

Discontinue use if signs of irritation or rash occur.

STOP USE

Discontinue use if signs of irritation or rash occur.

KEEP OUT OF REACH OF CHILDREN

Please keep out of reach of children. Do not swallow.

STORAGE AND HANDLING

Store in a cool and dry place.

INACTIVE INGREDIENT

WATER. GLYCERIN, ALLANTOIN

DOSAGE AND ADMINISTRATION

Clean and dry the skin, apply appropriate amount of this product evenly on the affected skin with warts, corns and calluses, and gently massage until absorbed.

INDICATIONS AND USAGE

Clean and dry the skin, apply appropriate amount of this product evenly on the affected skin with warts, corns and calluses, and gently massage until absorbed.